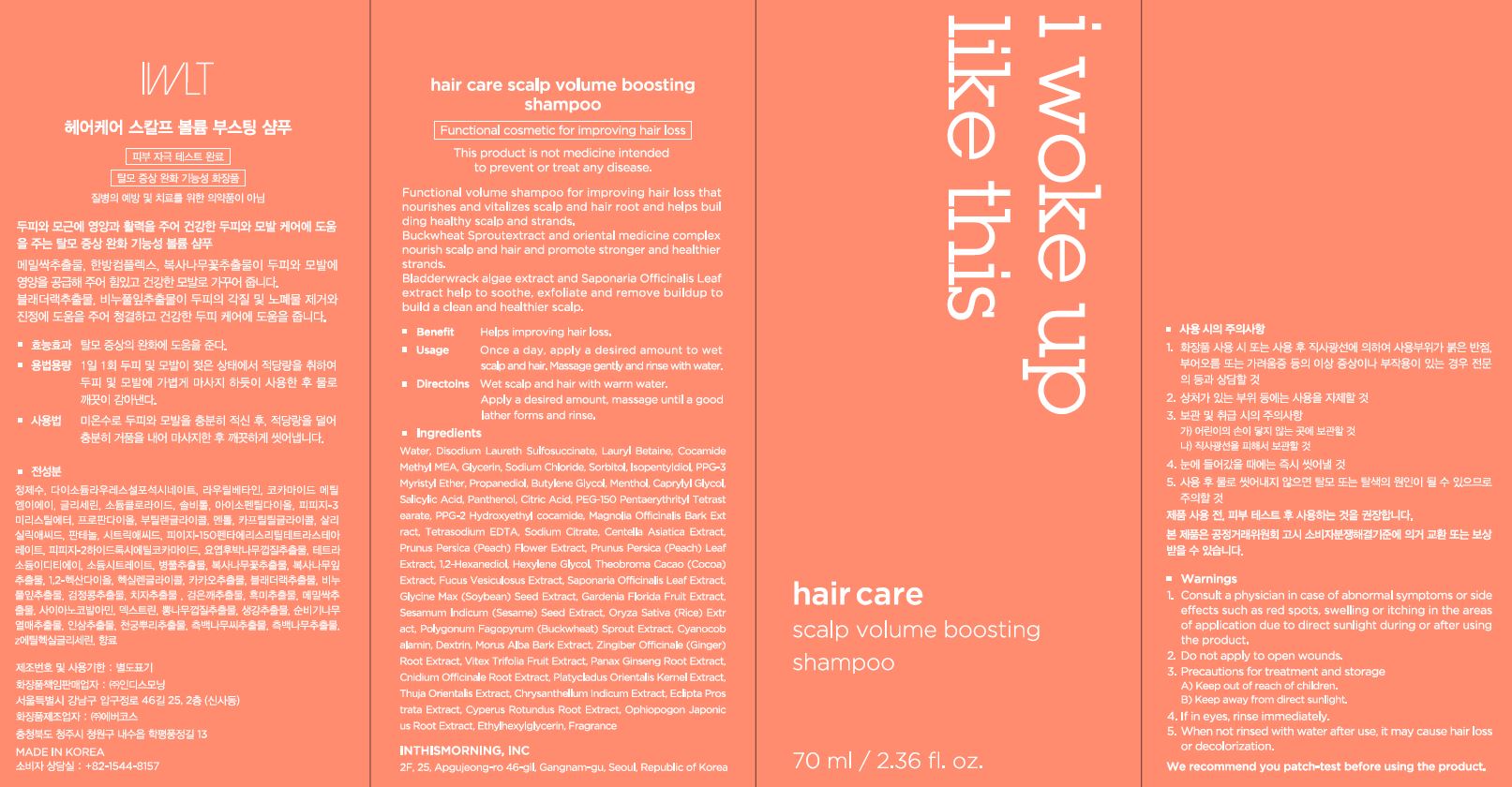 DRUG LABEL: Hair care scalp volume boostingshampoo
NDC: 71217-0067 | Form: SHAMPOO
Manufacturer: inthismorning co ltd
Category: otc | Type: HUMAN OTC DRUG LABEL
Date: 20230201

ACTIVE INGREDIENTS: RICE GERM 0.00055 g/100 mL
INACTIVE INGREDIENTS: WATER; GLYCERIN

Drug Facts

ACTIVE INGREDIENT

Polygonum Fagopyrum (Buckwheat) Sprout Extract

INACTIVE INGREDIENT

Water
Disodium Laureth Sulfosuccinate
Lauryl Betaine
Cocamide Methyl MEA
Glycerin
Sodium Chloride
Sorbitol
Isopentyldiol
PPG-3 Myristyl Ether
Propanediol
Butylene Glycol
Menthol
Caprylyl Glycol
Salicylic Acid
Panthenol
Citric Acid
PEG-150 Pentaerythrityl Tetrastearate
PPG-2 Hydroxyethyl cocamide
Magnolia Officinalis Bark Extract
Tetrasodium EDTA
Sodium Citrate
Centella Asiatica Extract
Prunus Persica (Peach) Flower Extract
Prunus Persica (Peach) Leaf Extract
1,2-Hexanediol
Hexylene Glycol
Theobroma Cacao (Cocoa) Extract
Fucus Vesiculosus Extract
Saponaria Officinalis Leaf Extract
Glycine Max (Soybean) Seed Extract
Gardenia Florida Fruit Extract
Sesamum Indicum (Sesame) Seed Extract
Oryza Sativa (Rice) Extract
Cyanocobalamin
Dextrin
Morus Alba Bark Extract
Zingiber Officinale (Ginger) Root Extract
Vitex Trifolia Fruit Extract
Panax Ginseng Root Extract
Cnidium Officinale Root Extract
Platycladus Orientalis Kernel Extract
Thuja Orientalis Extract
Chrysanthellum Indicum Extract
Eclipta Prostrata Extract
Cyperus Rotundus Root Extract
Ophiopogon Japonicus Root Extract
Ethylhexylglycerin
Fragrance

PURPOSE

scalp care

keep out or reach of the children

INDICATIONS AND USAGE

once a day, apply a desired amount to wet scalp and hair,

massage gently and rinse with water

WARNINGS

This product is for exeternal use only. Do not use for internal use
Storage and handling precautions
If possible, avoid direct sunlight and store in cool and area of low humidity in order to maintain the quality of the product and avoid misuse
Avoid placing the product near fire and store out in reach of children

- consult a physician in case of abnormal symptoms, such as red spots, swelling or itching, or side effects in the areas of application due to direct light during or after using the product

- do not use on wounded area

DOSAGE AND ADMINISTRATION

for external use only